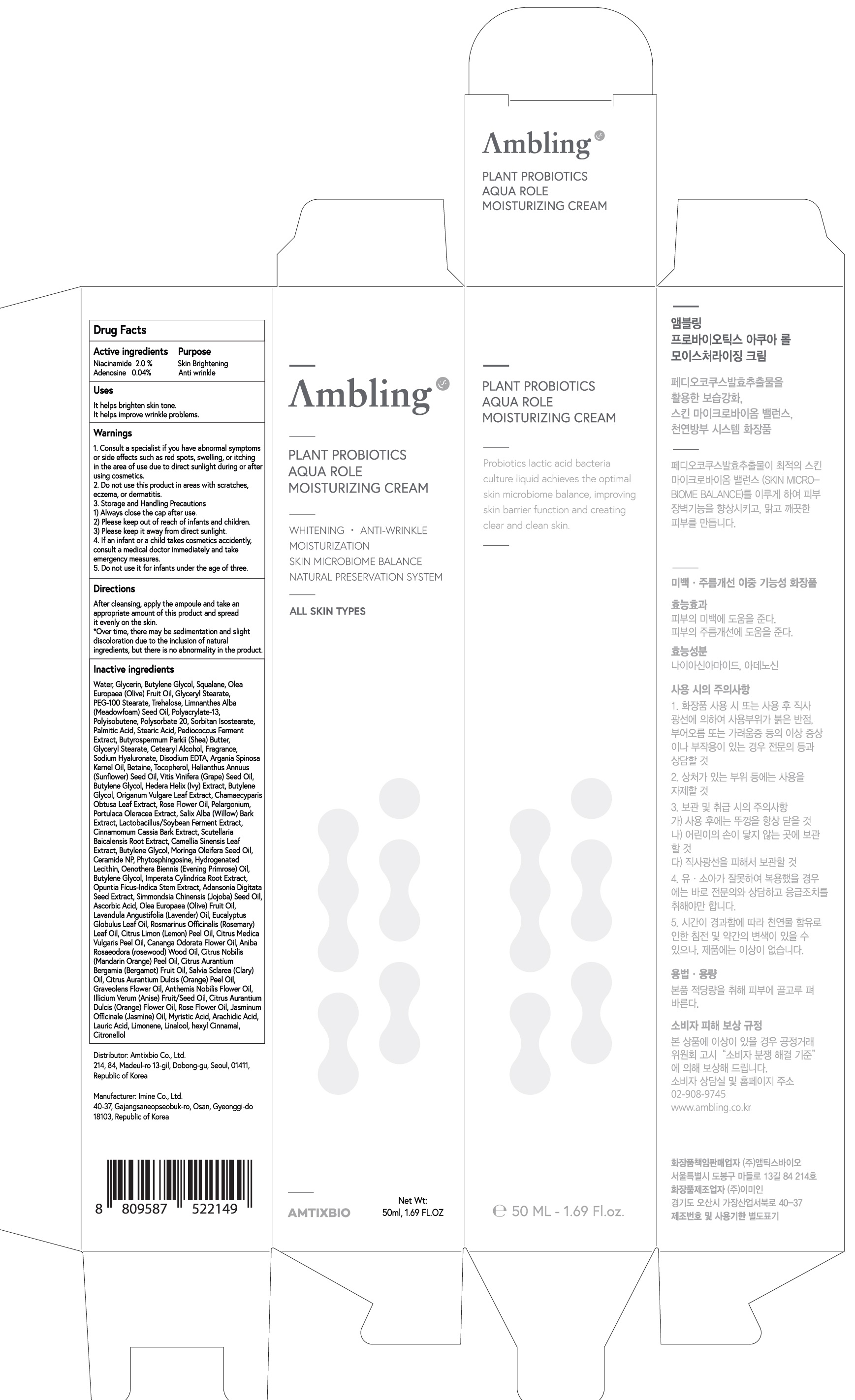 DRUG LABEL: Ambling Plant Probiotics Aqua Role Moisturizing
NDC: 73456-020 | Form: CREAM
Manufacturer: Amtixbio Co., Ltd.
Category: otc | Type: HUMAN OTC DRUG LABEL
Date: 20220216

ACTIVE INGREDIENTS: Niacinamide 1.00 g/50 mL; Adenosine 0.02 g/50 mL
INACTIVE INGREDIENTS: Water; Glycerin

ACTIVE INGREDIENTS

Niacinamide 2.0%, Adenosine 0.04%

INACTIVE INGREDIENTS

Water, Glycerin, Butylene Glycol, Squalane, Olea Europaea (Olive) Fruit Oil, Glyceryl Stearate, PEG-100 Stearate, Trehalose, Limnanthes Alba (Meadowfoam) Seed Oil, Polyacrylate-13, Polyisobutene, Polysorbate 20, Sorbitan Isostearate, Palmitic Acid, Stearic Acid, Pediococcus Ferment Extract, Butyrospermum Parkii (Shea) Butter, Glyceryl Stearate, Cetearyl Alcohol, Fragrance, Sodium Hyaluronate, Disodium EDTA, Argania Spinosa Kernel Oil, Betaine, Tocopherol, Helianthus Annuus (Sunflower) Seed Oil, Vitis Vinifera (Grape) Seed Oil, Butylene Glycol, Hedera Helix (Ivy) Extract, Butylene Glycol, Origanum Vulgare Leaf Extract, Chamaecyparis Obtusa Leaf Extract, Rose Flower Oil, Pelargonium, Portulaca Oleracea Extract, Salix Alba (Willow) Bark Extract, Lactobacillus/Soybean Ferment Extract, Cinnamomum Cassia Bark Extract, Scutellaria Baicalensis Root Extract, Camellia Sinensis Leaf Extract, Butylene Glycol, Moringa Oleifera Seed Oil, Ceramide NP, Phytosphingosine, Hydrogenated Lecithin, Oenothera Biennis (Evening Primrose) Oil, Butylene Glycol, Imperata Cylindrica Root Extract, Opuntia Ficus-Indica Stem Extract, Adansonia Digitata Seed Extract, Simmondsia Chinensis (Jojoba) Seed Oil, Ascorbic Acid, Olea Europaea (Olive) Fruit Oil, Lavandula Angustifolia (Lavender) Oil, Eucalyptus Globulus Leaf Oil, Rosmarinus Officinalis (Rosemary) Leaf Oil, Citrus Limon (Lemon) Peel Oil, Citrus Medica Vulgaris Peel Oil, Cananga Odorata Flower Oil, Aniba Rosaeodora (rosewood) Wood Oil, Citrus Nobilis (Mandarin Orange) Peel Oil, Citrus Aurantium Bergamia (Bergamot) Fruit Oil, Salvia Sclarea (Clary) Oil, Citrus Aurantium Dulcis (Orange) Peel Oil, Graveolens Flower Oil, Anthemis Nobilis Flower Oil, Illicium Verum (Anise) Fruit/Seed Oil, Citrus Aurantium Dulcis (Orange) Flower Oil, Rose Flower Oil, Jasminum Officinale (Jasmine) Oil, Myristic Acid, Arachidic Acid, Lauric Acid, Limonene, Linalool, hexyl Cinnamal, Citronellol

PURPOSE

Skin Brightening, Anti wrinkle

WARNINGS

1. Consult a specialist if you have abnormal symptoms or side effects such as red spots, swelling, or itching in the area of use due to direct sunlight during or after using cosmetics.

2. Do not use this product in areas with scratches, eczema, or dermatitis.

3. Storage and Handling Precautions
1) Always close the cap after use.
2) Please keep out of reach of infants and children.
3) Please keep it away from direct sunlight.

4. If an infant or a child takes cosmetics accidently, consult a medical doctor immediately and take emergency measures.

5. Do not use it for infants under the age of three.

KEEP OUT OF REACH OF CHILDREN

If an infant or a child takes cosmetics accidently, consult a medical doctor immediately and take emergency measures.

Uses

It helps brighten skin tone.
It helps improve wrinkle problems.

Directions

After cleansing, apply the ampoule and take an appropriate amount of this product and spread it evenly on the skin.

*Over time, there may be sedimentation and slight discoloration due to the inclusion of natural ingredients, but there is no abnormality in the product.